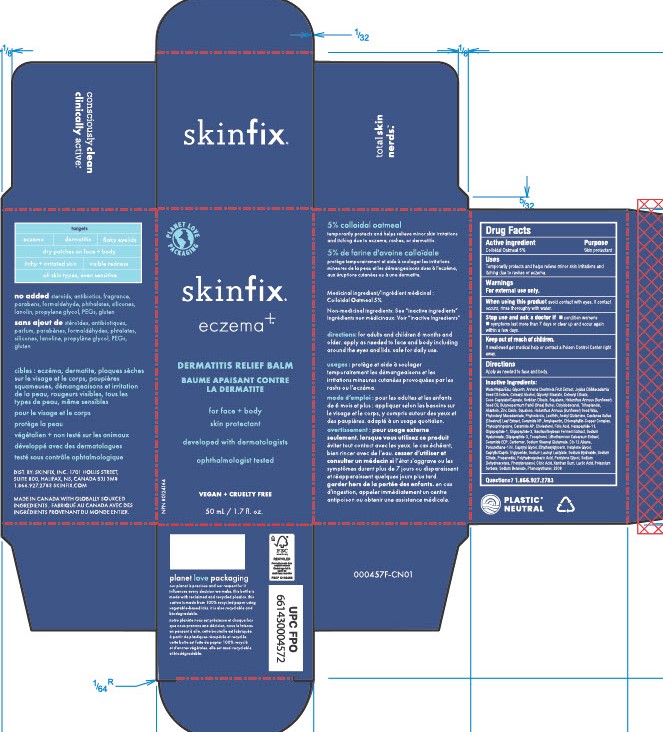 DRUG LABEL: ECZEMA DERMATITIS RELIEF BALM
NDC: 61328-112 | Form: CREAM
Manufacturer: Skinfix, Inc.
Category: otc | Type: HUMAN OTC DRUG LABEL
Date: 20260112

ACTIVE INGREDIENTS: OATMEAL 5 g/100 g
INACTIVE INGREDIENTS: SODIUM CITRATE; POLYHYDROXYSTEARIC ACID (2300 MW); AMYLOPECTIN, UNSPECIFIED SOURCE; PHENYLPROPANOL; PHYTOSTERYL MACADAMIATE; POTASSIUM SORBATE; SODIUM CHLORIDE; SODIUM CARBONATE; SODIUM BENZOATE; MACADAMIA SEED OIL GLYCERETH-8 ESTERS; HEXYLENE GLYCOL; LECITHIN, SOYBEAN; GLYCERIN; GLYCERYL MONOSTEARATE; SHEA BUTTER; HELIANTHUS ANNUUS SEED WAX; PENTYLENE GLYCOL; PHYTOSPHINGOSINE; HYALURONATE SODIUM; TOCOPHEROL; PHYMATOLITHON CALCAREUM; CETOSTEARYL ALCOHOL; COCO-CAPRYLATE/CAPRATE; SORBITAN OLIVATE; OCTYLDODECANOL; SQUALANE; SODIUM STEAROYL GLUTAMATE; ZINC OXIDE; SODIUM LAUROYL LACTYLATE; MEDIUM-CHAIN TRIGLYCERIDES; SODIUM HYDROXIDE; PROPANEDIOL; CASTANEA SATIVA LEAF; SODIUM COPPER CHLOROPHYLLIN; SODIUM DEHYDROACETATE; HEXAPEPTIDE-11; LACTIC ACID; CERAMIDE 1; WATER; TRIHEPTANOIN; ALLANTOIN; SQUALENE; CAPRYLYL GLYCOL; CHOLESTEROL; XANTHAN GUM; ETHYLHEXYLGLYCERIN; CETEARYL OLIVATE; SUNFLOWER OIL; PHENOXYETHANOL; CARBOMER HOMOPOLYMER, UNSPECIFIED TYPE; ACEGLUTAMIDE; CERAMIDE NP; CERAMIDE AP; FOLIC ACID; CITRIC ACID MONOHYDRATE; CHERIMOYA

ECZEMA DERMATITIS RELIEF BALM

ACTIVE INGREDIENT

Colloidal Oatmeal 5%

PURPOSE

Skin protectant

USES

Temporarily protects and helps relieve minor skin irritations and itching due to rashes or eczema.

WARNINGS

For external use only.

When using this product avoid contact with eyes. if contact occurs, rinse thoroughly with water.

KEEP OUT OF REACH OF CHILDREN

If swallowed get medical help or contact a poison control center right away.

STOP USE AND ASK A DOCTOR IF

- condition worsens
- symptoms last more than 7 days or clear up and occur again within a few days

DIRECTIONS

Apply as needed to face and body.

INACTIVE INGREDIENTS

Water/Aqua/Eau, Glycerin, Annona Cherimola Fruit Extract, Jojoba Oil/Macadamia Seed Oil Esters, Cetearyl Alcohol, Glyceryl Stearate, Cetearyl Olivate, Coco-Caprylate/Caprate, Sorbitan Olivate, Squalane, Helianthus Annuus (Sunflower) Seed Oil, Butyrospermum Parkii (Shea) Butter, Octyldodecanol, Triheptanoin, Allantoin, Zinc Oxide, Squalene, Helianthus Annuus (Sunflower) Seed Wax, Phytosteryl Macadamiate, Phytosterols, Lecithin, Acetyl Glutamine, Castanea Sativa (Chestnut) Leaf Extract, Ceramide NP, Amylopectin, Chlorophyllin-Copper Complex, Phytosphingosine, Ceramide AP, Cholesterol, Folic Acid, Hexapeptide-11, Oligopeptide-1, Oligopeptide-2, Bacillus/Soybean Ferment Extract, Sodium Hyaluronate, Oligopeptide-3, Tocopherol, Lithothamnion Calcareum Extract, Ceramide EOP, Carbomer, Sodium Stearoyl Glutamate, C9-12 Alkane, Polyurethane-100, Caprylyl Glycol, Ethylhexylglycerin, Hexylene Glycol, Caprylic/Capric Triglyceride, Sodium Lauroyl Lactylate, Sodium Hydroxide, Sodium Citrate, Propanediol, Polyhydroxystearic Acid, Pentylene Glycol, Sodium Dehydroacetate, Phenylpropanol, Citric Acid, Xanthan Gum, Lactic Acid, Sodium Carbonate, Sodium Chloride, Potassium Sorbate, Sodium Benzoate, Phenoxyethanol.

QUESTIONS?

1.866.927.2783